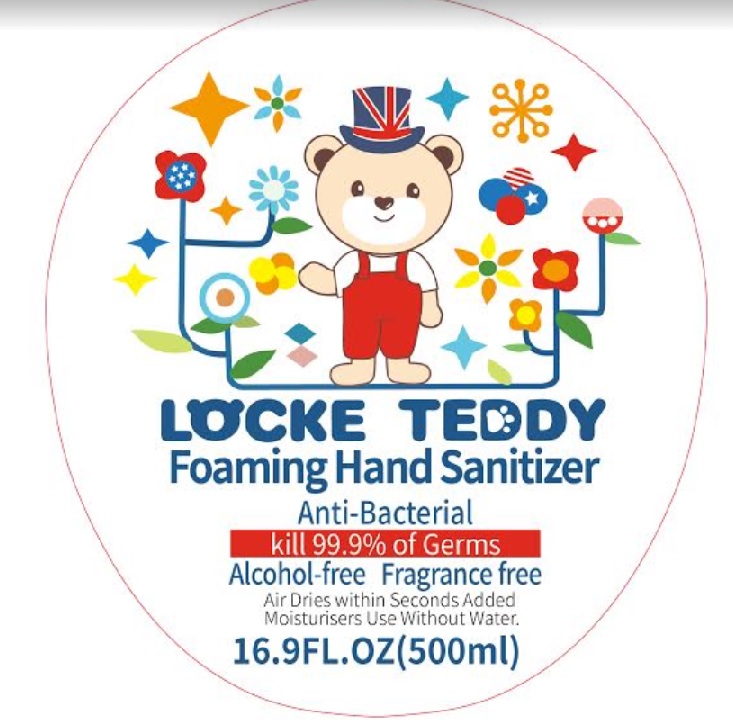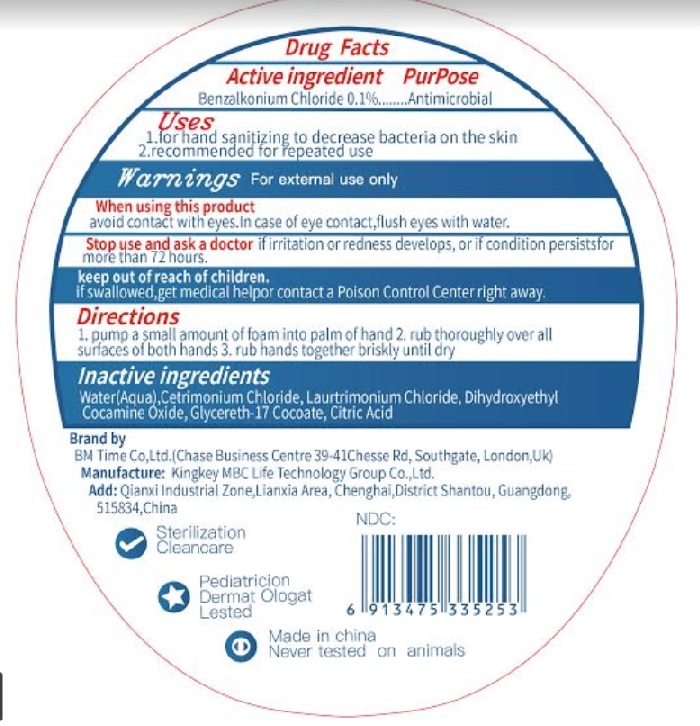 DRUG LABEL: LOCKE TEDDY Foaming Hand Sanitizer
NDC: 73928-011 | Form: SOLUTION
Manufacturer: KINGKEY MBC LIFE TECHNOLOGY GROUP CO., LTD
Category: otc | Type: HUMAN OTC DRUG LABEL
Date: 20251007

ACTIVE INGREDIENTS: BENZALKONIUM CHLORIDE 0.1 g/100 mL
INACTIVE INGREDIENTS: CETRIMONIUM CHLORIDE; LAURTRIMONIUM CHLORIDE; DIHYDROXYETHYL COCAMINE OXIDE; GLYCERETH-17 COCOATE; CITRIC ACID MONOHYDRATE; WATER

Active ingredient

Benzalkonium Chloride 0.1%

Purpose

Antimicrobial

Uses

1. for hand sanitizing to decrease the bacteria on the skin
2. recommended for repeated use

Warnings

For external use only.

When using this productavoid contact with eyes. In case of eye contact, flush eyes with water.

Stop use and ask a doctor ifirritation or redness develops, or if condition persists for more than 72 hours.

Keep out of reach of children

if swallowed, get medical help or contact a Poison Control Center right away.

Directions

1. pump a small amount of foam into palm of hand
2. rub thoroughly over all surfaces of both hands
3. rub hands together briskly until dry

Inactive ingredients

Water, cetrimonium chloride, Laurtrimonium chloride, Dihydroxyethyl Cocamine oxide, citric acid, glycereth-17 cocoate